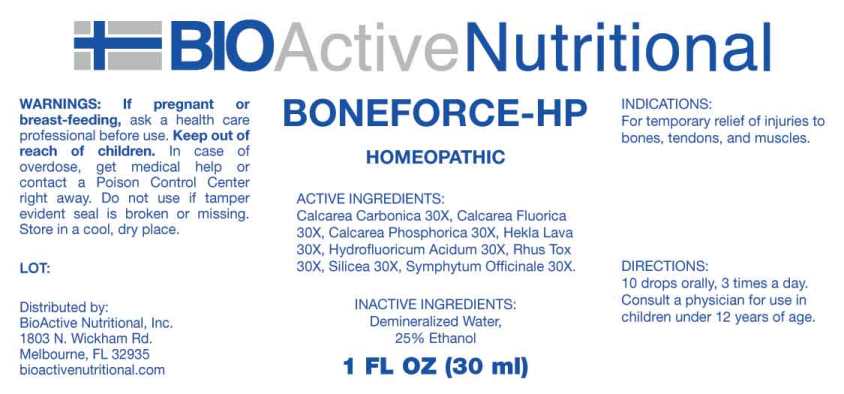 DRUG LABEL: Boneforce
NDC: 43857-0591 | Form: LIQUID
Manufacturer: BioActive Nutritional, Inc.
Category: homeopathic | Type: HUMAN OTC DRUG LABEL
Date: 20230607

ACTIVE INGREDIENTS: OYSTER SHELL CALCIUM CARBONATE, CRUDE 30 [hp_X]/1 mL; CALCIUM FLUORIDE 30 [hp_X]/1 mL; TRIBASIC CALCIUM PHOSPHATE 30 [hp_X]/1 mL; HEKLA LAVA 30 [hp_X]/1 mL; HYDROFLUORIC ACID 30 [hp_X]/1 mL; TOXICODENDRON PUBESCENS LEAF 30 [hp_X]/1 mL; SILICON DIOXIDE 30 [hp_X]/1 mL; COMFREY ROOT 30 [hp_X]/1 mL
INACTIVE INGREDIENTS: WATER; ALCOHOL

DRUG FACTS:

ACTIVE INGREDIENTS:

Calcarea Carbonica 30X, Calcarea Fluorica 30X, Calcarea Phosphorica 30X, Hekla Lava 30X, Hydrofluoricum Acidum 30X, Rhus Tox 30X, Silicea 30X, Symphytum Officinale 30X.

INDICATIONS:

For temporary relief of injuries to bones, tendons, and muscles.

WARNINGS:

If pregnant or breast-feeding, ask a health care professional before use.

Keep out of reach of children. In case of overdose, get medical help or contact a Poison Control Center right away.

Do not use if tamper evident seal is broken or missing.

Store in cool, dry place.

Keep out of reach of children. In case of overdose, get medical help or contact a Poison Control Center right away.

DIRECTIONS:

10 drops orally, 3 times a day. Consult a physician for use in children under 12 years of age.

INDICATIONS:

For temporary relief of injuries to bones, tendons, and muscles.

INACTIVE INGREDIENTS:

Demineralized Water, 25% Ethanol

QUESTIONS:

Distributed by:

BioActive Nutritional, Inc.

1803 N. Wickham Rd.

Melbourne, FL 32935

bioactivenutritional.com

PACKAGE LABEL DISPLAY:

BIOActive Nutritional

BONEFORCE-HP

HOMEOPATHIC

1 FL OZ (30 ml)